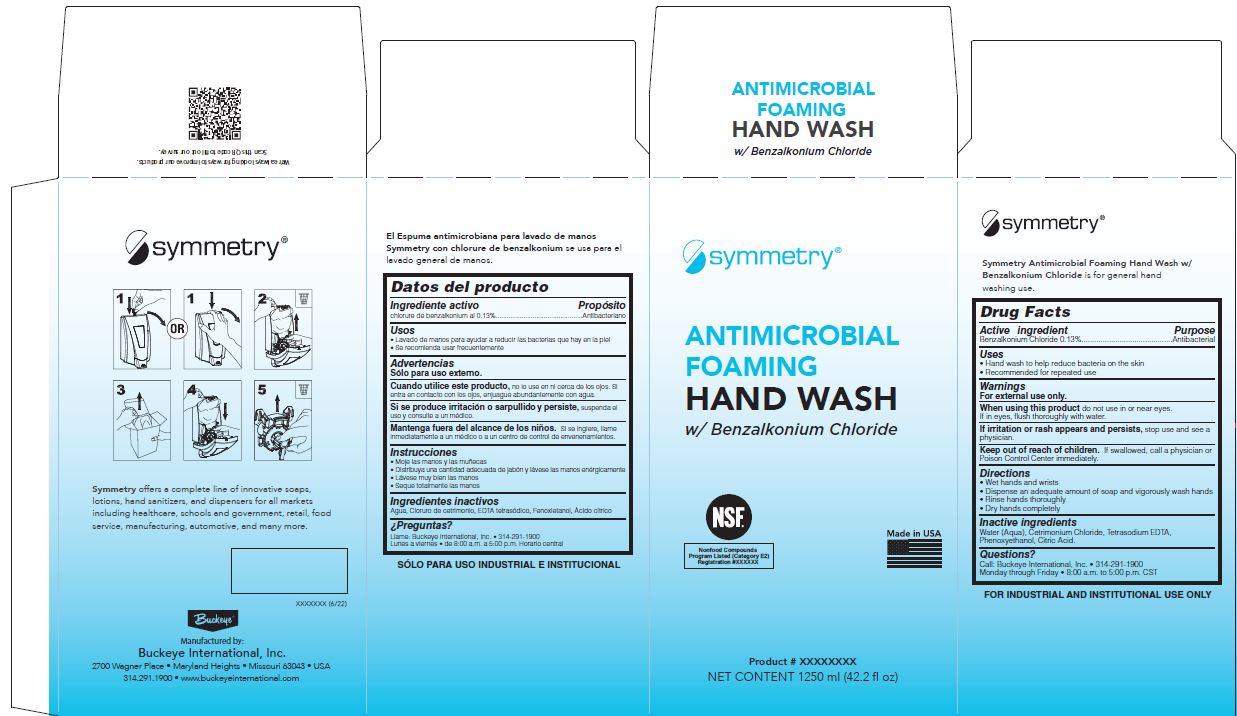 DRUG LABEL: SYMMETRY ANTIMICROBIAL FOAMING HAND WASH w/Benzalkonium Chloride
NDC: 30805-017 | Form: SOLUTION
Manufacturer: Buckeye International, Inc.
Category: otc | Type: HUMAN OTC DRUG LABEL
Date: 20241115

ACTIVE INGREDIENTS: BENZALKONIUM CHLORIDE 0.13 g/100 mL
INACTIVE INGREDIENTS: EDETATE SODIUM; PHENOXYETHANOL; WATER; CETRIMONIUM CHLORIDE; CITRIC ACID MONOHYDRATE

SYM BZK 0.13 30805-017

Active ingredient

Benzalkonium Choride 0.13%

Purpose

Antibacterial

Uses

- Hand wash to help reduce bacteria on the skin
- Recommended for repeated use

Warnings

For external use only.

WHEN USING

When using this productdo not use in or near eyes.

If in eyes, flush thoroughly with water.

STOP USE

If irritation or rash appears and persists, stop use and see a physician.

Keep out of reach of children. If swallowed, call a physician or Poison Control Center immediately.

Directions

- Wet hands and wrists
- Dispense an adequate amount of soap and vigorously wash hands
- Rinse hands thoroughly
- Dry hands completely

Inactive ingredients

Water (Aqua), Cetrimonium Chloride, Tetrasodium EDTA, Phenoxyethanol, Citric Acid

Questions?

Call: Buckeye International, Inc. 314-291-1900

Monday through Friday 8:00 a.m. to 5:00 p.m. CST

PACKAGE LABEL

Symmetry

Antimicrobial

Foaming

Hand Wash

w/ Benzakonium Chloride

NSF

Nonfood Compounds

Program Listed (Category E2)

Registration #XXXXXX

Made in USA

Product # XXXXXXXX

Net Content 1250 ml (42.2 fl oz)